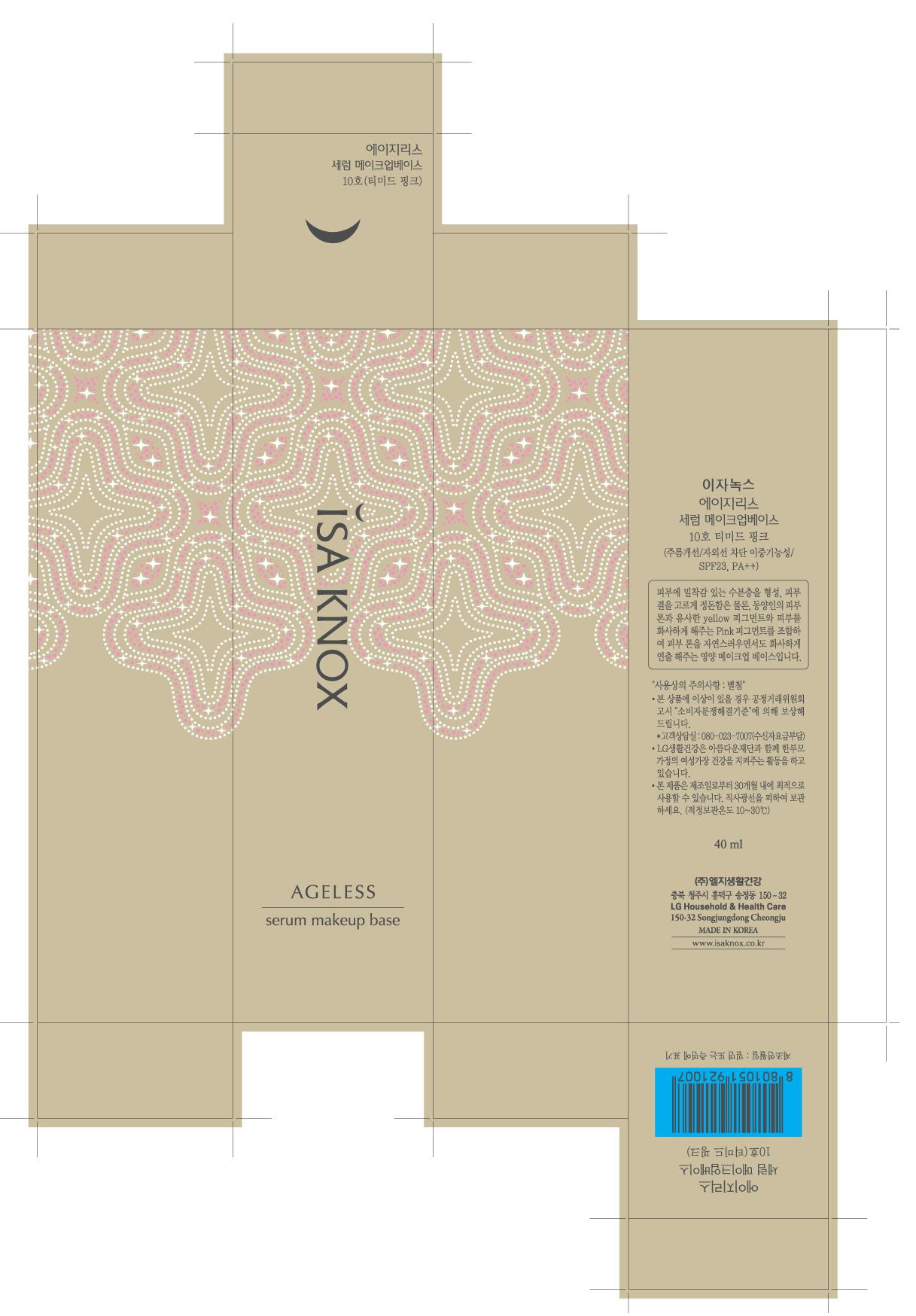 DRUG LABEL:  ISA KNOX AGELESS SERUM MAKEUP BASE 10
NDC: 53208-471 | Form: CREAM
Manufacturer: LG Household and Healthcare, Inc.
Category: otc | Type: HUMAN OTC DRUG LABEL
Date: 20120514

ACTIVE INGREDIENTS: OCTINOXATE 3 mL/100 mL; TITANIUM DIOXIDE 3.38 mL/100 mL; DIMETHICONE 0.08 mL/100 mL; ALUMINUM HYDROXIDE 0.18 mL/100 mL; STEARIC ACID 0.18 mL/100 mL; HYDROXYPROLINE 0.53 mL/100 mL
INACTIVE INGREDIENTS: WATER; CYCLOMETHICONE 5; CYCLOMETHICONE; ISODODECANE; MAGNESIUM SULFATE; PHENOXYETHANOL; METHYLPARABEN; PROPYLPARABEN; ETHYLPARABEN; .ALPHA.-TOCOPHEROL ACETATE, D-

Drug Facts

Active Ingredients

OCTINOXATE 3ml/100ml

TITANIUM DIOXIDE 3.38ml/100ml

DIMETHICONE 0.08ml/100ml

ALUMINUM HYDROXIDE 0.18ml/100ml

STEARIC ACID 0.18ml/100ml

HYDROXYPROLINE 0.53ml/100ml

WARNINGS AND PRECAUTIONS

For external use only.

Keep out of reach of children. Is swallowed, get medical help or contact a Poison Control Center right away.

WHEN USING

Keep out of eyes. Rinse with water to remove.

Package Label

Isaknox

Ageless

Make Up Base

Number 10